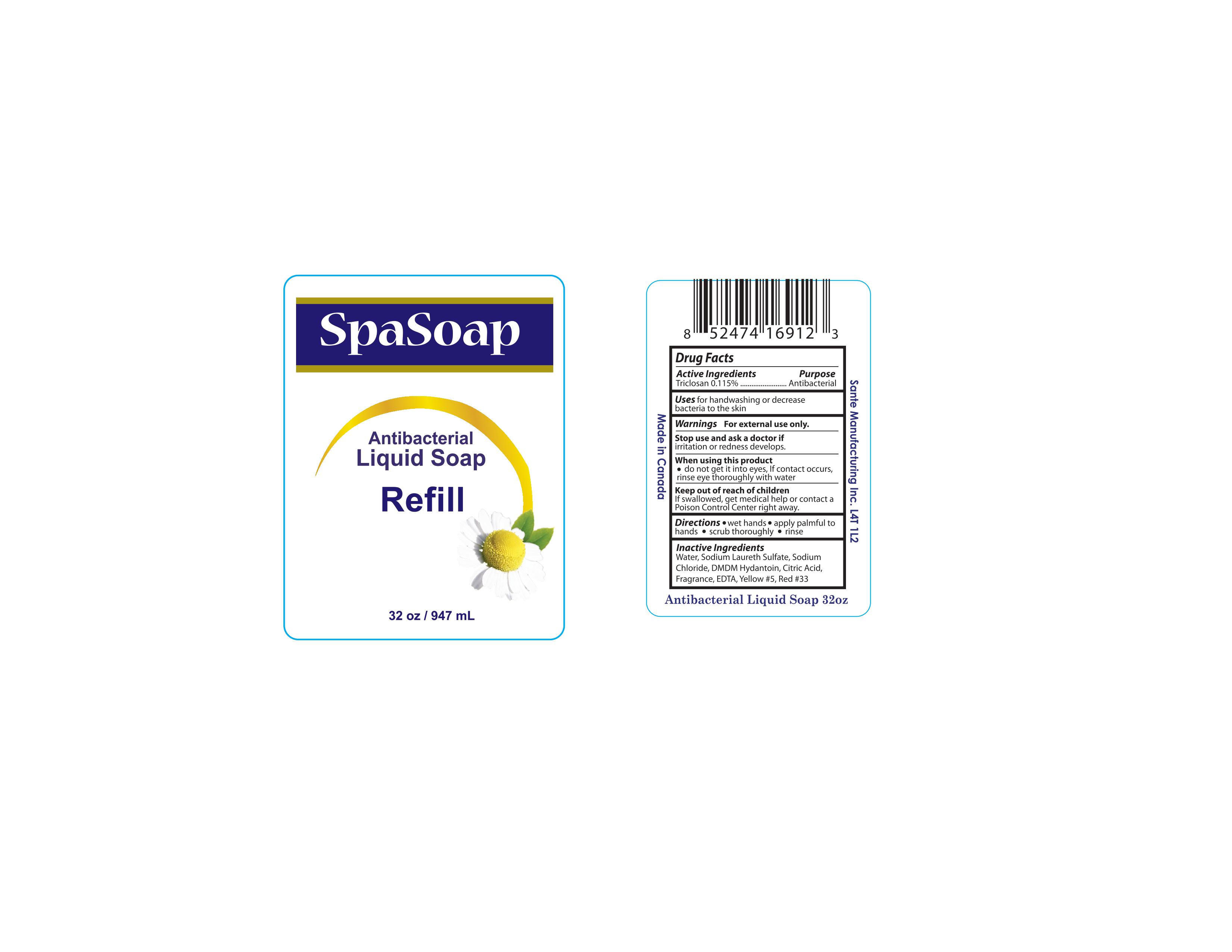 DRUG LABEL: Antibacterial
NDC: 71020-007 | Form: LIQUID
Manufacturer: Sante Manufacturing Inc
Category: otc | Type: HUMAN OTC DRUG LABEL
Date: 20161019

ACTIVE INGREDIENTS: TRICLOSAN 1.15 mg/1 mL
INACTIVE INGREDIENTS: WATER; DMDM HYDANTOIN; EDETIC ACID; FD&C YELLOW NO. 5; FD&C RED NO. 3; SODIUM LAURETH SULFATE; SODIUM CHLORIDE; ANHYDROUS CITRIC ACID

Active Ingredients - Triclosan 0.115%

Purpose - Antibacterial

INDICATIONS AND USAGE

Uses for handwashing or decrease bacteria to the skin

Stop use and ask a doctor if irritation or redness develops

When using this product

- do not get it into eyes. If contact occurs, rinse eye thoroughly with water

Keep out of reach of children If swallowed, get medical help or contact a Poison Control Center right away

Directions

- Wet hands
- apply palmful to hands
- scrub thoroughly
- rinse

INACTIVE INGREDIENT

Water, Sodium Laureth Sulfate, Sodium Chloride, DMDM Hydantoin, Citric Acid, Fragrance, EDTA, Yellow#5, Red#33

WARNINGS

Warning For external use only